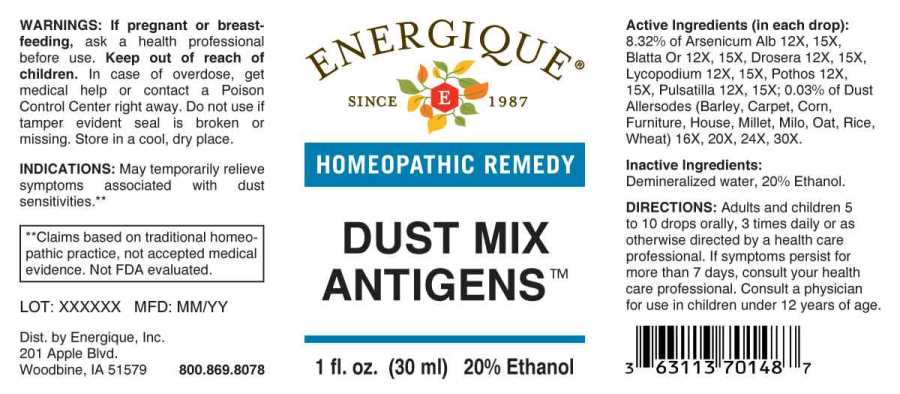 DRUG LABEL: Dust Mix Antigens
NDC: 44911-0541 | Form: LIQUID
Manufacturer: Energique, Inc.
Category: homeopathic | Type: HUMAN OTC DRUG LABEL
Date: 20240422

ACTIVE INGREDIENTS: ARSENIC TRIOXIDE 12 [hp_X]/1 mL; BLATTA ORIENTALIS 12 [hp_X]/1 mL; DROSERA ROTUNDIFOLIA WHOLE 12 [hp_X]/1 mL; LYCOPODIUM CLAVATUM SPORE 12 [hp_X]/1 mL; SYMPLOCARPUS FOETIDUS ROOT 12 [hp_X]/1 mL; PULSATILLA PRATENSIS WHOLE 12 [hp_X]/1 mL; BARLEY 16 [hp_X]/1 mL; CORN 16 [hp_X]/1 mL; HOUSE DUST 16 [hp_X]/1 mL; MILLET 16 [hp_X]/1 mL; SORGHUM BICOLOR WHOLE 16 [hp_X]/1 mL; OAT 16 [hp_X]/1 mL; BROWN RICE 16 [hp_X]/1 mL; WHEAT 16 [hp_X]/1 mL
INACTIVE INGREDIENTS: WATER; ALCOHOL

DRUG FACTS:

ACTIVE INGREDIENTS:

(in each drop): 8.32% of Arsenicum Album 12X, 15X, Blatta Orientalis 12X, 15X, Drosera (Rotundifolia) 12X, 15X, Lycopodium Clavatum 12X, 15X, Pothos Foetidus 12X, 15X, Pulsatilla (PRatensis) 12X, 15X; 0.03% of Barley 16X, 20X, 24X, 30X, Corn 16X, 20X, 24X, 30X, House 16X, 20X, 24X, 30X, Millet 16X, 20X, 24X, 30X, Milo 16X, 20X, 24X, 30X, Oat 16X, 20X, 24X, 30X, Rice 16X, 20X, 24X, 30X, Carpet 16X, 20X, 24X, 30X, Furniture 16X, 20X, 24X, 30X, Wheat 16X, 20X, 24X, 30X.

INDICATIONS:

May temporarily relieve symptoms associated with dust sensitivites.**

**Claims based on traditional homeopathic practice, not accepted medical evidence. Not FDA evaluated.

WARNINGS:

If pregnant or breast-feeding, ask a health professional before use.

Keep out of reach of children. In case of overdose, get medical help or contact a Poison Control Center right away.

Do not use if tamper evident seal is broken or missing.

Store in a cool, dry place.

KEEP OUT OF REACH OF CHILDREN:

In case of overdose, get medical help or contact a Poison Control Center right away.

DIRECTIONS:

Adults and children 5 to 10 drops orally, 3 times daily or as otherwise directed by a health care professional. If symptoms persist for more than 7 days, consult your health care professional. Consult a physician for use in children under 12 years of age.

INDICATIONS:

May temporarily relieve symptoms associated with dust sensitivites.**

**Claims based on traditional homeopathic practice, not accepted medical evidence. Not FDA evaluated.

INACTIVE INGREDIENTS:

Demineralized water, 20% Ethanol.

QUESTIONS:

Dist. by Energique, Inc.

201 Apple Blvd

Woodbine, IA 51579

800.869.8078

PACKAGE LABEL DISPLAY:

ENERGIQUE
SINCE 1987
HOMEOPATHIC REMEDY
DUST MIX
ANTIGENS
1 fl. oz. (30 ml)